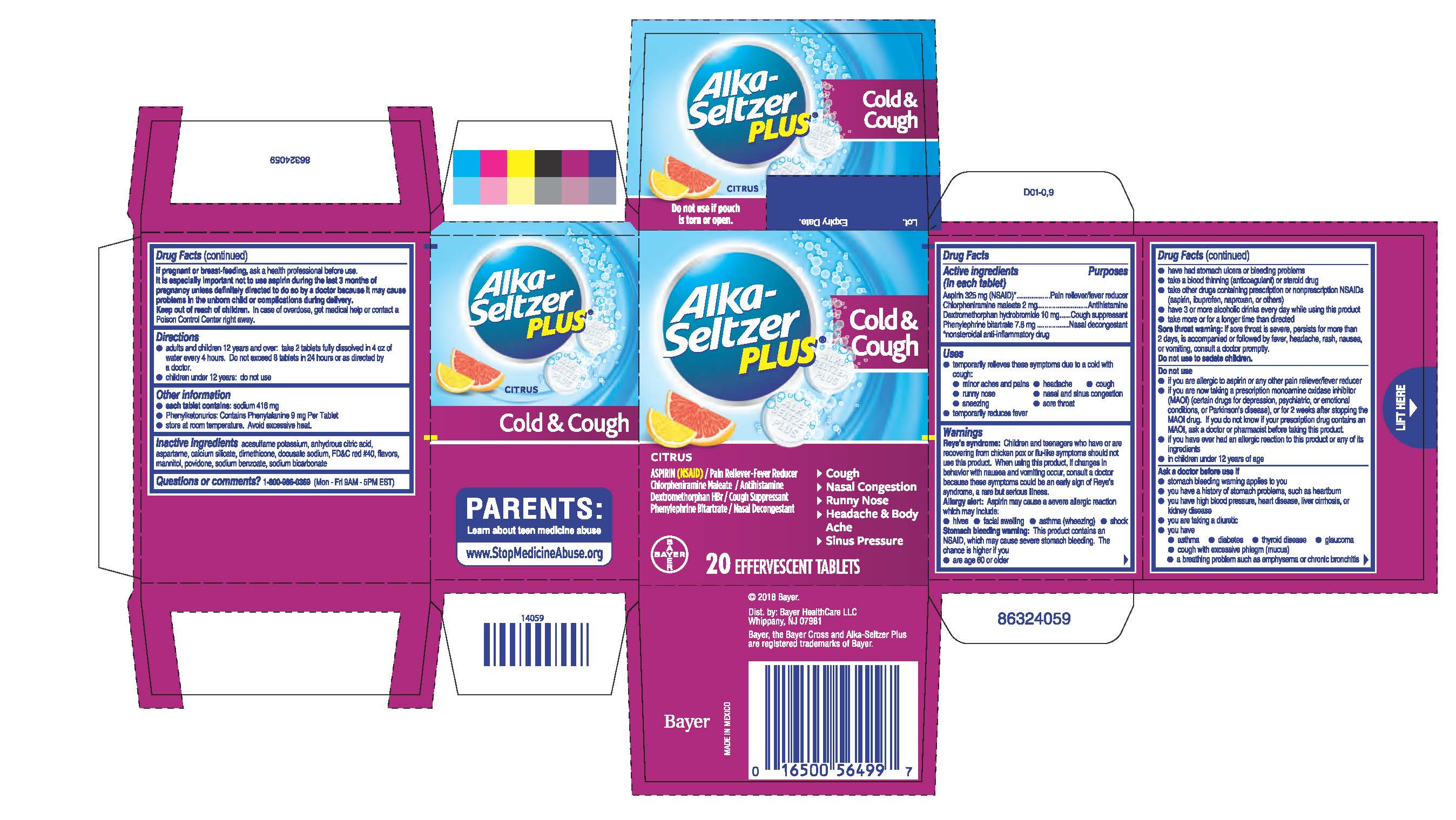 DRUG LABEL: Alka-Seltzer Plus Cold and Cough
NDC: 0280-1555 | Form: TABLET, EFFERVESCENT
Manufacturer: Bayer HealthCare LLC.
Category: otc | Type: HUMAN OTC DRUG LABEL
Date: 20251204

ACTIVE INGREDIENTS: ASPIRIN 325 mg/1 1; CHLORPHENIRAMINE MALEATE 2 mg/1 1; DEXTROMETHORPHAN HYDROBROMIDE 10 mg/1 1; PHENYLEPHRINE BITARTRATE 7.8 mg/1 1
INACTIVE INGREDIENTS: DIMETHICONE; SODIUM BICARBONATE; DOCUSATE SODIUM; MANNITOL; POVIDONE; SODIUM BENZOATE; CALCIUM SILICATE; FD&C RED NO. 40; ACESULFAME POTASSIUM; ANHYDROUS CITRIC ACID; ASPARTAME

Alka-Seltzer Plus® Cold & Cough Effervescent Tablets

Drug Facts

Active ingredients (in each tablet)

Aspirin 325 mg (NSAID)*

Chlorpheniramine maleate 2 mg

Dextromethorphan hydrobromide 10 mg

Phenylephrine bitartrate 7.8 mg

*nonsteroidal anti-inflammatory drug

Purposes

Pain reliever/fever reducer

Antihistamine

Cough suppressant

Nasal decongestant

Uses

 temporarily relieves these symptoms due to a cold with cough:

 ·minor aches and pains  ·headache  ·cough

 ·runny nose  ·nasal and sinus congestion

 ·sneezing  ·sore throat

 ·temporarily reduces fever

Warnings

Reye’s syndrome: Children and teenagers who have or are

recovering from chicken pox or flu-like symptoms should not use this

product. When using this product, if changes in behavior with nausea

and vomiting occur, consult a doctor because these symptoms could be

an early sign of Reye’s syndrome, a rare but serious illness.

Allergy alert: Aspirin may cause a severe allergic reaction which may

include:

 hives  facial swelling  asthma (wheezing)  shock

Stomach bleeding warning: This product contains an NSAID, which

may cause severe stomach bleeding. The chance is higher if you

● are age 60 or older

● have had stomach ulcers or bleeding problems

● take a blood thinning (anticoagulant) or steroid drug

● take other drugs containing prescription or nonprescription NSAIDs

(aspirin, ibuprofen, naproxen, or others)

● have 3 or more alcoholic drinks every day while using this product

● take more or for a longer time than directed

Sore throat warning: If sore throat is severe, persists for more than

2 days, is accompanied or followed by fever, headache, rash, nausea,

or vomiting, consult a doctor promptly.

Do not use to sedate children.

Do not use

● if you are allergic to aspirin or any other pain reliever/fever reducer

● if you are now taking a prescription monoamine oxidase inhibitor

(MAOI) (certain drugs for depression, psychiatric, or emotional

conditions, or Parkinson's disease), or for 2 weeks after stopping

the MAOI drug. If you do not know if your prescription drug contains

an MAOI, ask a doctor or pharmacist before taking this product.

● if you have ever had an allergic reaction to this product or any of its

ingredients

● in children under 12 years of age

Ask a doctor before use if

● stomach bleeding warning applies to you

● you have a history of stomach problems, such as heartburn

● you have high blood pressure, heart disease, liver cirrhosis,

or kidney disease

● you are taking a diuretic

● you have:

● asthma ● diabetes ● thyroid disease ● glaucoma

● cough with excessive phlegm (mucus)

● a breathing problem such as emphysema or chronic bronchitis

● difficulty in urination due to enlargement of the prostate gland

● persistent or chronic cough such as occurs with smoking, asthma,

or emphysema

● a sodium-restricted diet

When using this product

● do not exceed recommended dosage

 may cause marked drowsiness

● avoid alcoholic drinks

● excitability may occur, especially in children

● alcohol, sedatives, and tranquilizers may increase drowsiness

● be careful when driving a motor vehicle or operating machinery

Stop use and ask a doctor if

● an allergic reaction occurs. Seek medical help right away.

● you experience any of the following signs of stomach bleeding

● feel faint ● vomit blood ● have bloody or black stools

● have stomach pain that does not get better

 pain, cough, or nasal congestion gets worse or lasts more than 7 days

 fever gets worse or lasts more than 3 days

 redness or swelling is present

 new symptoms occur

 ringing in the ears or a loss of hearing occurs

 cough comes back or occurs with rash or headache that lasts. These

could be signs of a serious condition.

 nervousness, dizziness, or sleeplessness occurs

PREGNANCY OR BREAST FEEDING

If pregnant or breast-feeding, ask a health professional before use.

It is especially important not to use aspirin during the last 3

months of pregnancy unless definitely directed to do so by a

doctor because it may cause problems in the unborn child or

complications during delivery.

Keep out of reach of children. In case of overdose, get medical help

or contact a Poison Control Center right away.

Directions

● adults and children 12 years and over: take 2 tablets fully dissolved

in 4 oz of water every 4 hours. Do not exceed 8 tablets in 24 hours

or as directed by a doctor.

● children under 12 years: do not use

Other information

● each tablet contains: sodium 416 mg

● Phenylketonurics: Contains Phenylalanine 9 mg Per Tablet

● store at room temperature. Avoid excessive heat.

Inactive ingredients acesulfame potassium, anhydrous citric

acid, aspartame, calcium silicate, dimethicone, docusate sodium, FD&C

red #40, flavors, mannitol, povidone, sodium benzoate, sodium

bicarbonate

Questions or comments?1-800-986-0369 (Mon - Fri 9AM -

5PM EST)

PACKAGE LABEL

Alka-Seltzer

PLUS®

Cold &

Cough

CITRUS

ASPIRIN (NSAID) / Pain Reliever/Fever Reducer

Chlorpheniramine Maleate/Antihistamine

Dextromethorphan HBr/Cough Suppresant

Phenylephrine Bitartrate/Nasal Decongestant

- Cough
- Nasal Congestion
- Runny Nose
- Headache & Body Ache
- Sinus Pressure

20 EFFERVESCENT TABLETS